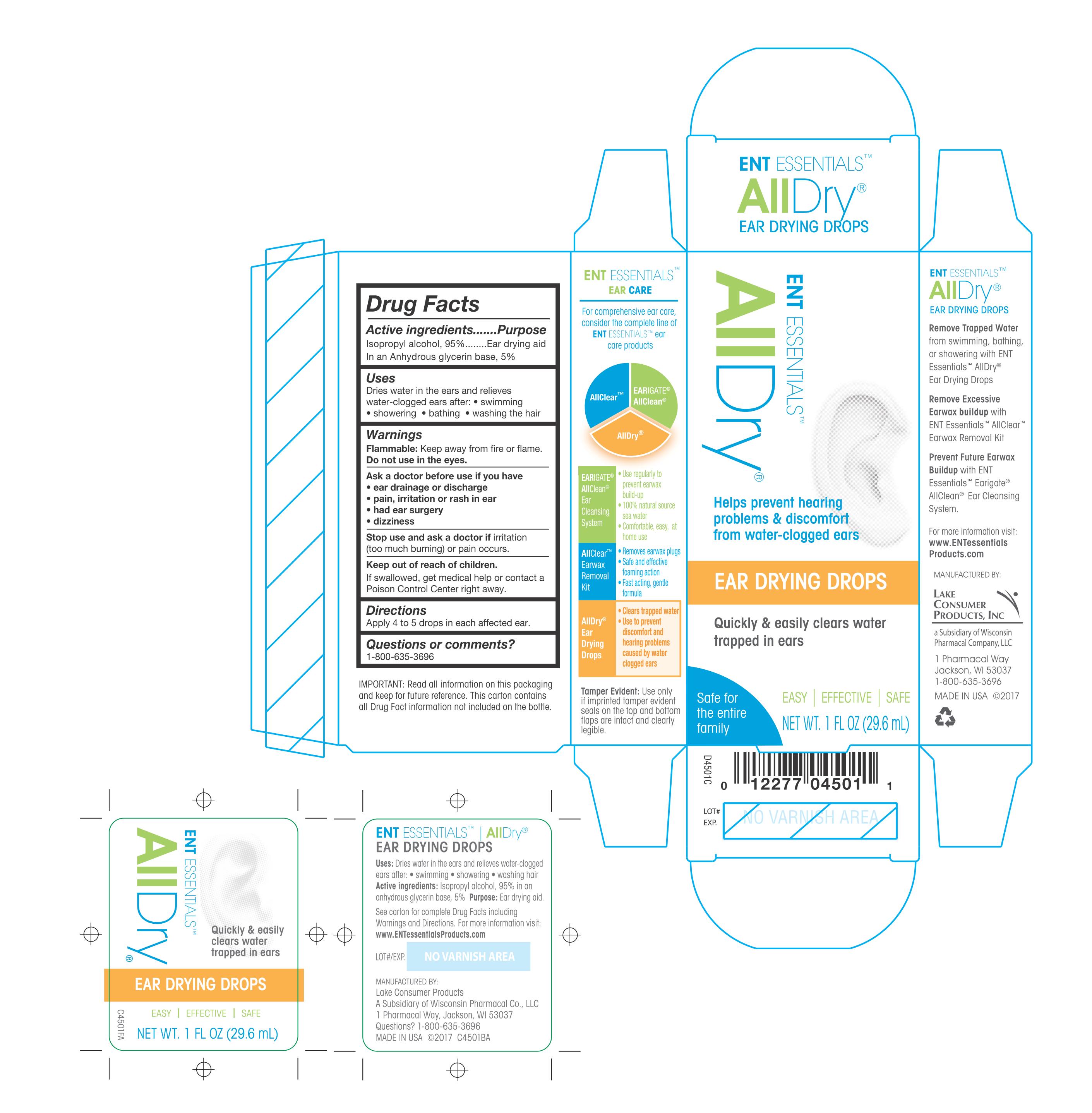 DRUG LABEL: ENT Essentials All Dry Ear Drying Drops
NDC: 68093-4501 | Form: LIQUID
Manufacturer: Wisconsin Pharmacal Company
Category: otc | Type: HUMAN OTC DRUG LABEL
Date: 20171128

ACTIVE INGREDIENTS: ISOPROPYL ALCOHOL 0.95 g/100 g
INACTIVE INGREDIENTS: GLYCERIN

Active Ingredients

Isopropyl alcohol, 95%

Purpose

Ear Drying aid in an Anhydrous glycerin base, 5%

Uses

Dries water in the ears and relieves water-clogged ears after:

- swimming
- showering
- bathing
- washing the hair

Warnings

Flammable:Keep away from fire or flame.

Do not use in the eyes.

Ask a doctor before use if you have

- ear drainage or dischage
- pain, irritiaon, or rash in ear
- had ear surgery
- dizziness

Stop use and aks a doctor if irritation (too much burning) or pain occurs

Keep our of reach of children

If swallowed, get medical help or contact a Poison Control Center right away.

Directions

Apply 4 to 5 drops in each affected ear.

Questions or comments?

1-800-635-3696